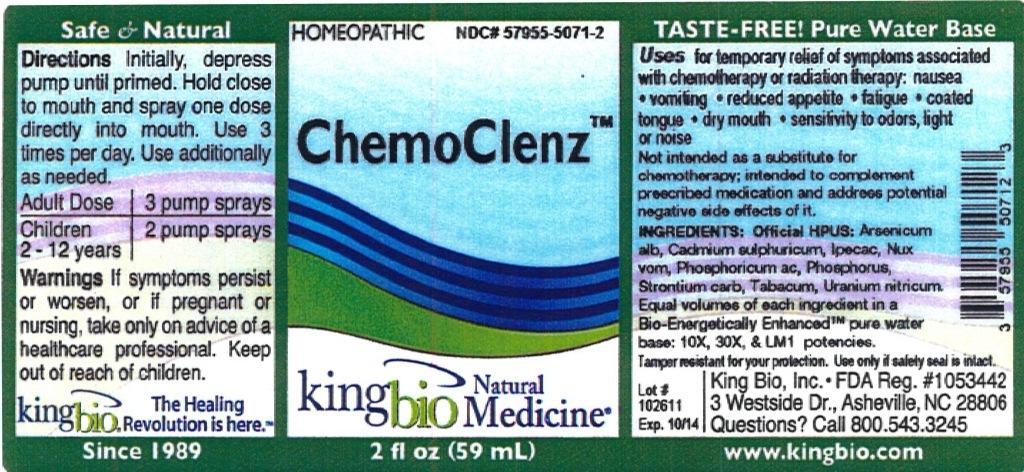 DRUG LABEL: ChemoClenz
                
NDC: 57955-5071 | Form: LIQUID
Manufacturer: King Bio, Inc.
Category: homeopathic | Type: HUMAN OTC DRUG LABEL
Date: 20120905

ACTIVE INGREDIENTS: ARSENIC TRIOXIDE 10 [hp_X]/59 mL; CADMIUM SULFATE 10 [hp_X]/59 mL; IPECAC 10 [hp_X]/59 mL; STRYCHNOS NUX-VOMICA SEED 10 [hp_X]/59 mL; PHOSPHORIC ACID 10 [hp_X]/59 mL; PHOSPHORUS 10 [hp_X]/59 mL; STRONTIUM CARBONATE 10 [hp_X]/59 mL; TOBACCO LEAF 10 [hp_X]/59 mL; URANYL NITRATE HEXAHYDRATE 10 [hp_X]/59 mL
INACTIVE INGREDIENTS: WATER

ChemoClenz

Active Ingredients

Official HPUS: Arsenicum album, Cadmium sulphuricum, Ipecacuanha, Nux vomica, Phosphoricum acidum, Phosphorus, Strontium carbonicum, Tabacum, Uranium nitricum.

Inactive Ingredient

Equal volumes of each ingredient in a Bio-Energetically Enhanced pure water base: 10X, 30X, and LM1 potencies.

Purposes

Uses for temporary relief of symptoms associated with chemotherapy or radiation therapy:

- nausea
- vomiting
- reduced appetite
- fatigue
- coated tongue
- dry mouth
- sensitivity to odors, light or noise

Not intended as a substitute for chemotherapy, intended to complement prescribed medication and address potential negative side effects of it.

Directions

Initially, depress pump until primed. Hold close to mouth and spray one dose directly into mouth. Use 3 times per day. Use additionally as needed.

Adult dose - 3 pump sprays

Children 2-12 years - 2 pump sprays

Warnings

Warnings If symptoms persist or worsen, or if pregnant or nursing, take only on advice of a healthcare professional.

Tamper resistant for your protection. Use only if safety seal is intact.

Keep out of reach of children.

Uses

For the temporary relief of symptoms associated with chemotherapy or radiation therapy: nausea, vomiting, reduced appetite, fatigue, coated tongue, dry mouth, sensitivity to odors, light or noise. Not intended as a substitute for chemotherapy; intended to complement prescribed medication and address potential negative side effects of it.

PACKAGE LABEL

King Bio, Inc.

3 Westside Dr.

Asheville, NC 28806

Questions? 800.543.3245

www.kingbio.com

Reference image: chemoclenz.jpg